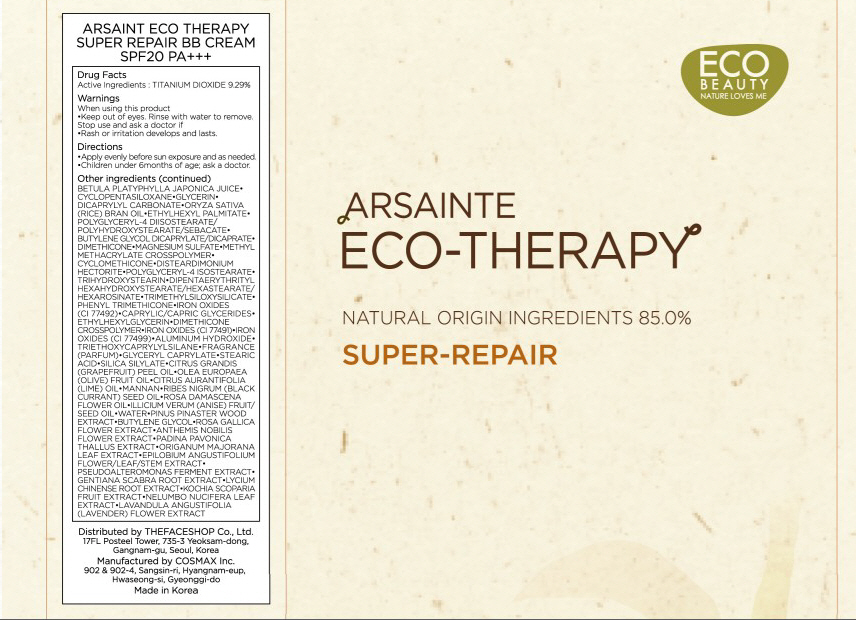 DRUG LABEL: ARSAINTE ECO THERAPY SUPER REPAIR BB
NDC: 51523-001 | Form: CREAM
Manufacturer: THEFACESHOP CO., LTD.
Category: otc | Type: HUMAN OTC DRUG LABEL
Date: 20100712

ACTIVE INGREDIENTS: TITANIUM DIOXIDE 4.64 mL/50 mL

Drug Facts

Active Ingredient: TITANIUM DIOXIDE

Inactive Ingredients:
BETULA PLATYPHYLLA JAPONICA JUICE, CYCLOPENTASILOXANE, GLYCERIN, DICAPRYLYL CARBONATE, ORYZA, SATIVA (RICE) BRAN OIL, ETHYLHEXYL PALMITATE, POLYGLYCERYL-4 DIISOSTEARATE/POLYHYDROXYSTEARATE/SEBACATE, BUTYLENE GLYCOL DICAPRYLATE/DICAPRATE, DIMETHICONE, MAGNESIUM SULFATE, METHYL
METHACRYLATE CROSSPOLYMER, CYCLOMETHICONE, DISTEARDIMONIUM HECTORITE, POLYGLYCERYL-4 ISOSTEARATE, TRIHYDROXYSTEARIN, DIPENTAERYTHRITYL HEXAHYDROXYSTEARATE/HEXASTEARATE/HEXAROSINATE, TRIMETHYLSILOXYSILICATE, PHENYL TRIMETHICONE, IRON OXIDES (CI 77492), CAPRYLIC/CAPRIC GLYCERIDES, ETHYLHEXYLGLYCERIN, DIMETHICONE CROSSPOLYMER, IRON OXIDES (CI 77491), IRON OXIDES (CI 77499), ALUMINUM HYDROXIDE, TRIETHOXYCAPRYLYLSILANE, FRAGRANCE, GLYCERYL CAPRYLATE, STEARIC ACID, SILICA SILYLATE, CITRUS GRANDIS (GRAPEFRUIT) PEEL OIL, OLEA EUROPAEA (OLIVE) FRUIT OIL, CITRUS AURANTIFOLIA (LIME) OIL, MANNAN, RIBES NIGRUM (BLACK CURRANT) SEED OIL, ROSA DAMASCENA FLOWER OIL, ILLICIUM VERUM (ANISE) FRUIT/SEED OIL, WATER, PINUS PINASTER WOOD EXTRACT, BUTYLENE GLYCOL, ROSA GALLICA FLOWER EXTRACT, ANTHEMIS NOBILIS FLOWER EXTRACT, PADINA PAVONICA THALLUS EXTRACT, ORIGANUM MAJORANA LEAF EXTRACT, EPILOBIUM ANGUSTIFOLIUM FLOWER/LEAF/STEM EXTRACT, PSEUDOALTEROMONAS FERMENT EXTRACT, GENTIANA SCABRA ROOT EXTRACT, LYCIUM CHINENSE ROOT
EXTRACT, KOCHIA SCOPARIA FRUIT EXTRACT, NELUMBO NUCIFERA LEAF EXTRACT, LAVANDULA ANGUSTIFOLIA (LAVENDER) FLOWER EXTRACT

Warnings:
When using this product
Keep out of eyes. Rinse with water to remove.
Stop use and ask a doctor if
Rash or irritation develops and lasts.
Directions:
Apply evenly before sun exposure and as needed.
Children under 6months of age; ask a doctor.